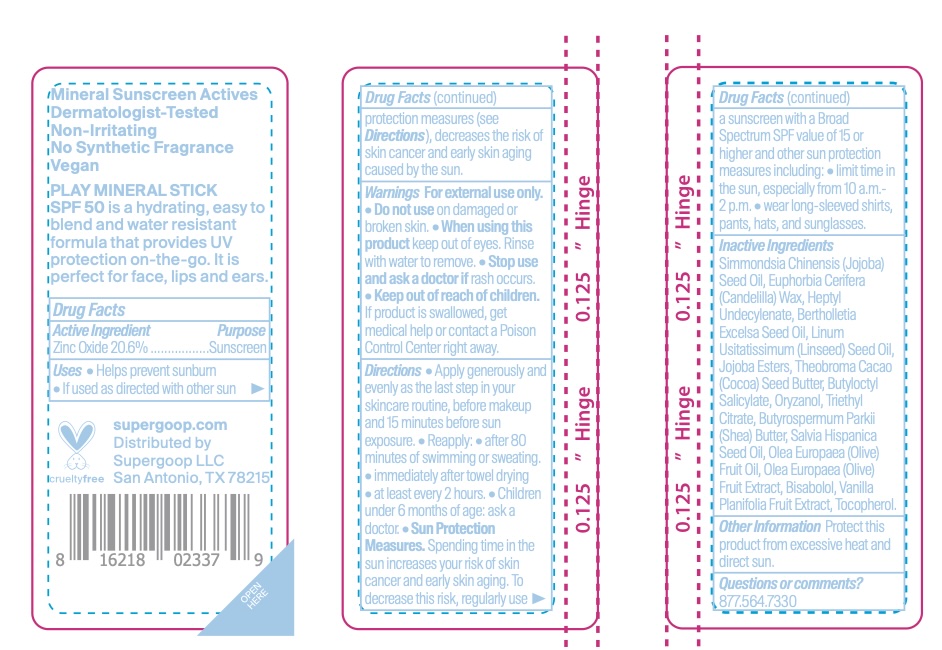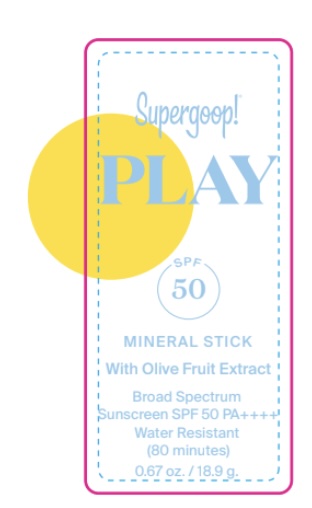 DRUG LABEL: PLAY Mineral Stick SPF 50 with Olive Fruit Extract
NDC: 75936-657 | Form: STICK
Manufacturer: Supergoop LLC
Category: otc | Type: HUMAN OTC DRUG LABEL
Date: 20250818

ACTIVE INGREDIENTS: ZINC OXIDE 20.6 g/100 g
INACTIVE INGREDIENTS: OLEA EUROPAEA (OLIVE) FRUIT OIL; SQUALENE; VANILLA BEAN; HEPTYL UNDECYLENATE; LINUM USITATISSIMUM (LINSEED) SEED OIL; BUTYROSPERMUM PARKII (SHEA) BUTTER; TOCOPHEROL; BUTYLOCTYL SALICYLATE; ORYZANOL; BISABOLOL; TRIETHYL CITRATE; HELIANTHUS ANNUUS (SUNFLOWER) SEED OIL; BETA-SITOSTEROL; SALVIA HISPANICA SEED OIL; OLEA EUROPAEA (OLIVE) FRUIT; SIMMONDSIA CHINENSIS (JOJOBA) SEED OIL; EUPHORBIA CERIFERA (CANDELILLA) WAX; BRAZIL NUT OIL; THEOBROMA CACAO (COCOA) SEED BUTTER

PLAY Mineral Stick SPF 50 with Olive Fruit Extract

Active Ingredients: Zinc Oxide 20.6%

PURPOSE

Helps prevent sunburn

If used as directed with other sun protection measures (see Directions), decreases the risk of skin cancer and early skin aging caused by the sun

WARNINGS

For External use only

Do not use on damaged or broken skin

When using this product, keep out of eyes. Rinse with water to remove

Stop use and ask a doctor if rash occurs

Keep out of reach of children. If product is swallowed, get medical help, or contact a poison control center right away.

Directions

• Apply generously and evenly as the last step in your skincare routine, before makeup and 15 minutes before sun exposure. • Reapply: • after 80 minutes of swimming or sweating. • immediately after towel drying • at least every 2 hours. • Children under 6 months of age: ask a doctor. • Sun Protection Measures. Spending time in the sun increases your risk of skin cancer and early skin aging. To decrease this risk, regularly use a sunscreen with a Broad Spectrum SPF value of 15 or higher and other sun protection measures including: • limit time in the sun, especially from 10 a.m.-2 p.m. • wear long-sleeved shirts, pants, hats, and sunglasses.

INACTIVE INGREDIENT

Inactive Ingredients: Simmondsia Chinensis (Jojoba) Seed Oil, Euphorbia Cerifera (Candelilla) Wax, Heptyl Undecylenate, Bertholletia Excelsa Seed Oil, Linum Usitatissimum (Linseed) Seed Oil, Jojoba Esters, Theobroma Cacao (Cocoa) Seed Butter, Butyloctyl Salicylate, Oryzanol, Triethyl Citrate, Butyrospermum Parkii (Shea) Butter, Salvia Hispanica Seed Oil, Olea Europaea (Olive) Fruit Oil, Olea Europaea (Olive) Fruit Extract, Bisabolol, Vanilla Planifolia Fruit Extract, Tocopherol

PACKAGE LABEL

PLAY

SPF 50

MINERAL STICK

With Olive Fruit Extract

Broad Spectrum

Sunscreen SPF 50 PA++++

Water Resistant

(80 minutes)

0.67 oz. / 18.9 g.